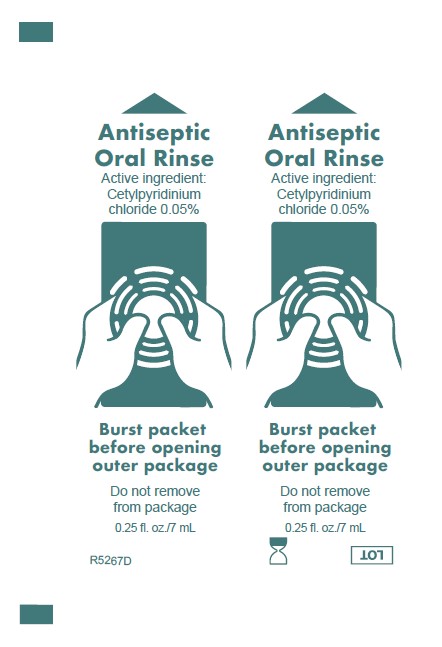 DRUG LABEL: Antiseptic Oral Rinse
NDC: 53462-175 | Form: MOUTHWASH
Manufacturer: Sage Products LLC
Category: otc | Type: HUMAN OTC DRUG LABEL
Date: 20251208

ACTIVE INGREDIENTS: CETYLPYRIDINIUM CHLORIDE 0.5 mg/1 mL
INACTIVE INGREDIENTS: SORBITOL; PEPPERMINT; POTASSIUM SORBATE; POLYSORBATE 80; POLYSORBATE 20; CITRIC ACID MONOHYDRATE; FD&C BLUE NO. 1; WATER

Antiseptic Oral Rinse

Active ingredient

Cetylpyridinium chloride .05%

Purpose

Antiseptic Rinse

Use

Helps reduce chance of infection in minor oral irritation.

Stop use and ask a doctor if:
• Sore mouth symptoms do not improve in 7 days.
• Swelling, rash or fever develops.
• Irritation, pain or redness persists or worsens.

Keep out of reach of children.
If more than used for antisepsis is accidentally swallowed, get medical help or contact a Poison Control Center right away.

Directions

- Use up to 4 times daily or as directed by a dentist or doctor.
- Adults and children 3 years and over: rinse mouth for approx. one minute with 1/2 Tbsp., or use topically (dip into bottle) with clean Toothette® Oral Swab. Instruct to expectorate.
- Children under 12 years of age: supervise use.
- Children under 3 years of age: consult a dentist or doctor.

Inactive Ingredients

Water, sorbitol, peppermint flavor, potassium sorbate, polysorbate 80, polysorbate 20, citric acid, Blue 1 (CI42090)

Questions?

Call toll free 800-323-2220